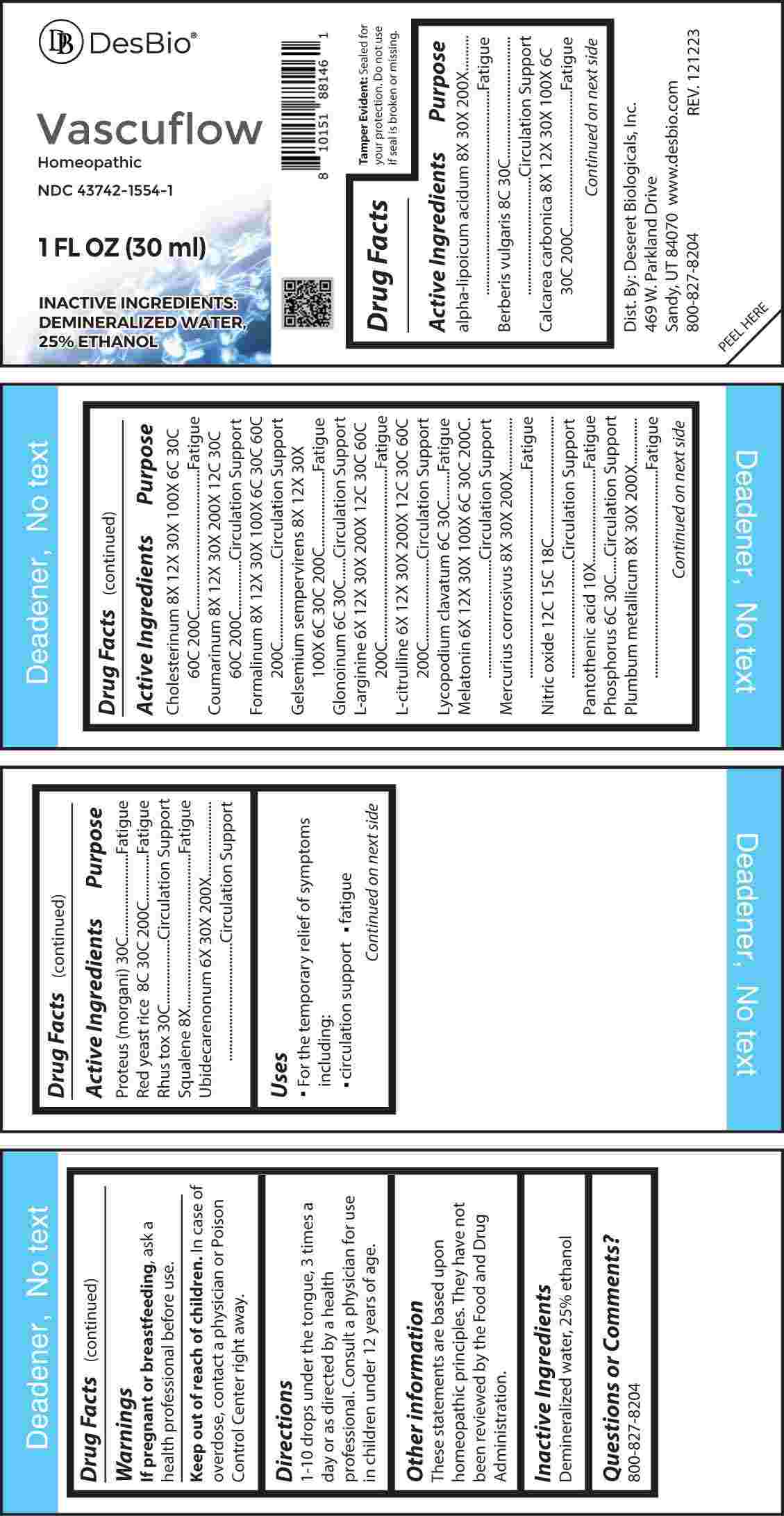 DRUG LABEL: Vascuflow
NDC: 43742-1554 | Form: LIQUID
Manufacturer: Deseret Biologicals, Inc.
Category: homeopathic | Type: HUMAN OTC DRUG LABEL
Date: 20240402

ACTIVE INGREDIENTS: MELATONIN 6 [hp_X]/1 mL; ARGININE 6 [hp_X]/1 mL; CITRULLINE 6 [hp_X]/1 mL; UBIDECARENONE 6 [hp_X]/1 mL; SQUALENE 8 [hp_X]/1 mL; OYSTER SHELL CALCIUM CARBONATE, CRUDE 8 [hp_X]/1 mL; CHOLESTEROL 8 [hp_X]/1 mL; COUMARIN 8 [hp_X]/1 mL; FORMALDEHYDE 8 [hp_X]/1 mL; GELSEMIUM SEMPERVIRENS ROOT 8 [hp_X]/1 mL; THIOCTIC ACID 8 [hp_X]/1 mL; MERCURIC CHLORIDE 8 [hp_X]/1 mL; LEAD 8 [hp_X]/1 mL; PANTOTHENIC ACID 10 [hp_X]/1 mL; NITROGLYCERIN 6 [hp_C]/1 mL; LYCOPODIUM CLAVATUM SPORE 6 [hp_C]/1 mL; PHOSPHORUS 6 [hp_C]/1 mL; BERBERIS VULGARIS ROOT BARK 8 [hp_C]/1 mL; MONASCUS PURPUREUS 8 [hp_C]/1 mL; NITRIC OXIDE 12 [hp_C]/1 mL; PROTEUS MORGANII 30 [hp_C]/1 mL; TOXICODENDRON PUBESCENS LEAF 30 [hp_C]/1 mL
INACTIVE INGREDIENTS: WATER; ALCOHOL

DRUG FACTS:

ACTIVE INGREDIENTS:

Alpha-Lipoicum Acidum 8X, 30X, 200X, Berberis Vulgaris 8C, 30C, Calcarea Carbonica 8X, 12X, 30X, 100X, 6C, 30C, 200C, Cholesterinum 8X, 12X, 30X, 100X, 6C, 30C, 60C, 200C, Coumarinum 8X, 12X, 30X, 200X, 12C, 30C, 60C, 200C, Formalinum 8X, 12X, 30X, 100X, 6C, 30C, 60C, 200C, Gelsemium Sempervirens 8X, 12X, 30X, 100X, 6C, 30C, 200C, Glonoinum 6C, 30C, L-Arginine 6X, 12X, 30X, 200X, 12C, 30C, 60C, 200C, L-Citrulline 6X, 12X, 30X, 200X, 12C, 30C, 60C, 200C, Lycopodium Clavatum 6C, 30C, Melatonin 6X, 12X, 30X, 100X, 6C, 30C, 200C, Mercurius Corrosivus 8X, 30X, 200X, Nitric Oxide 12C, 15C, 18C, Pantothenic Acid 10X, Phosphorus 6C, 30C, Plumbum Metallicum 8X, 30X, 200X, Proteus (Morgani) 30C, Red Yeast Rice 8C, 30C, 200C, Rhus Tox 30C, Squalene 8X, Ubidecarenonum 6X, 30X, 200X.

PURPOSE:

Alpha-Lipoicum Acidum - Fatigue, Berberis Vulgaris – Circulation Support, Calcarea Carbonica - Fatigue, Cholesterinum - Fatigue, Coumarinum – Circulation Support, Formalinum – Circulation Support, Gelsemium Sempervirens - Fatigue, Glonoinum – Circulation Support, L-Arginine - Fatigue, L-Citrulline – Circulation Support, Lycopodium Clavatum - Fatigue, Melatonin – Circulation Support, Mercurius Corrosivus - Fatigue, Nitric Oxide – Circulation Support, Pantothenic Acid - Fatigue, Phosphorus – Circulation Support, Plumbum Metallicum - Fatigue, Proteus (Morgani) - Fatigue, Red Yeast Rice - Fatigue, Rhus Tox – Circulation Support, Squalene - Fatigue, Ubidecarenonum – Circulation Support

USES:

• For the temporary relief of the symptoms including:

• circulation support • fatigue

These statements are based upon homeopathic principles. They have not been reviewed by the Food and Drug Administration.

WARNINGS:

If pregnant or breast-feeding, ask a health professional before use.

Keep out of reach of children. In case of overdose, contact a physician or Poison Control Center right away.

Tamper Evident: Sealed for your protection. Do not use if seal is broken or missing.

KEEP OUT OF REACH OF CHILDREN:

In case of overdose, contact a physician or Poison Control Center right away.

DIRECTIONS:

1-10 drops under the tongue, 3 times a day or as directed by a health professional. Consult a physician for use in children under 12 years of age.

INACTIVE INGREDIENTS:

Demineralized water, 25% ethanol

QUESTIONS:

Dist. By: Deseret Biologicals, Inc.
469 W. Parkland Drive
Sandy, UT 84070

www.desbio.com

800-827-8204

PACKAGE LABEL DISPLAY:

Des Bio

Vascuflow

Homeopathic

NDC 43742-1554-1

1 FL OZ (30 ml)